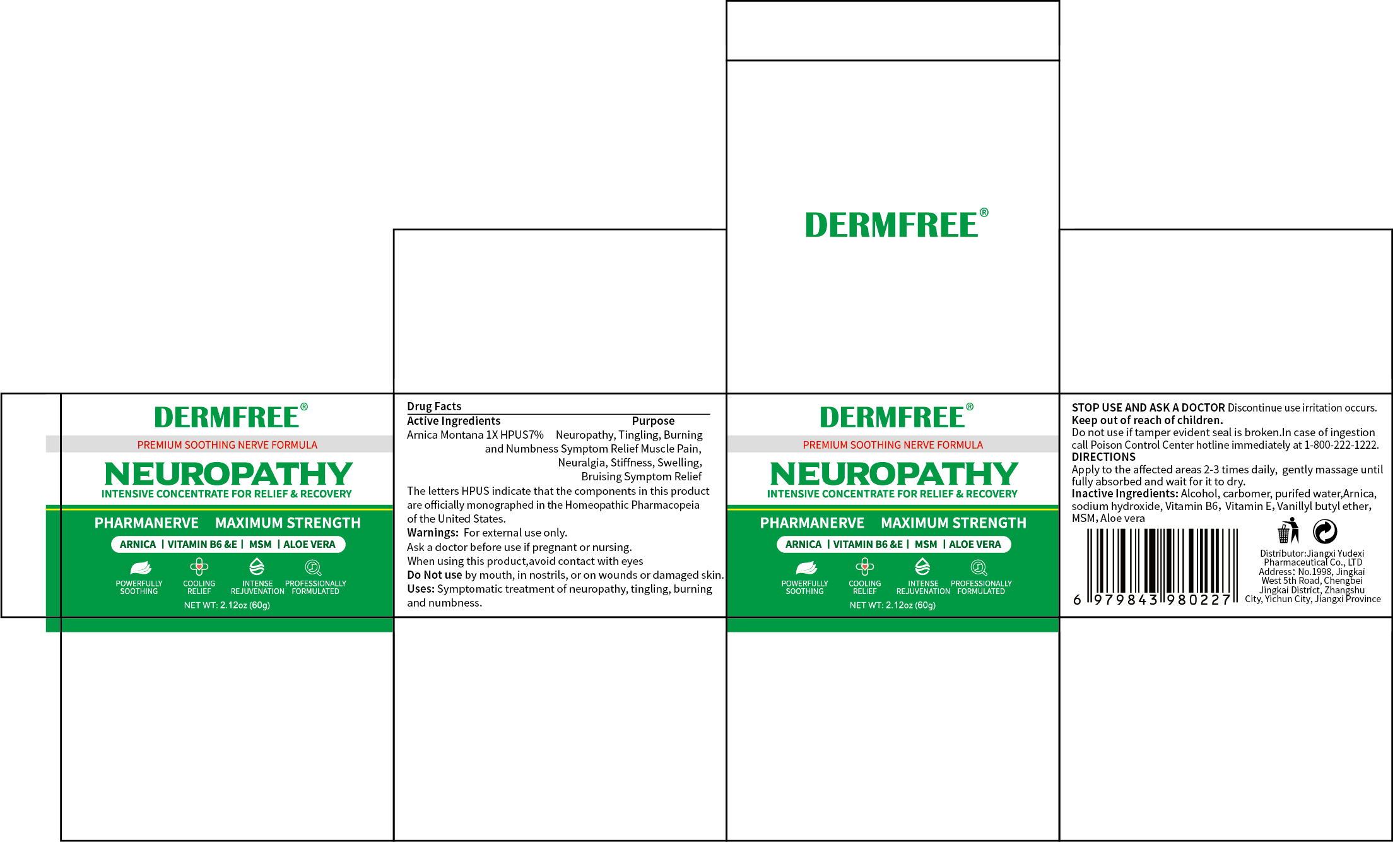 DRUG LABEL: DERMFREE NEUROPATHY
NDC: 85248-124 | Form: CREAM
Manufacturer: Jiangxi Yudexi Pharmaceutical Co., LTD
Category: otc | Type: HUMAN OTC DRUG LABEL
Date: 20260208

ACTIVE INGREDIENTS: ARNICA MONTANA 7 g/100 g
INACTIVE INGREDIENTS: SODIUM HYDROXIDE; CARBOMER; WATER; VANILLYL BUTYL ETHER; ALOE VERA LEAF; ALCOHOL; ARNICA MONTANA FLOWER; TOCOPHERYL SUCCINATE; DIMETHYL SULFONE; PYRIDOXINE

85248-124

Active Ingredient

Arnica Montana 1X HPUS 7%

Purpose

Neuropathy, Tingling, Burning and Numbness Symptom Relief Muscle Pain, Neuralgia, Stiffness, Swelling， Bruising Symptom Relief

Use

Symptomatic treatment of neuropathy, tingling， burning and numbness.

Warnings

For external use only.
Ask a doctor before use if pregnant or nursing.
When using this product, avoid contact with eyes.

Do not use

by mouth, in nostrils, or on wounds or damaged skin.if tamper evident seal is broken.

When Using

When using this product,avoid contact with eyes

Stop Use

Discontinue use if irritation occurs.

Ask Doctor

Discontinue use if irritation occurs. Ask a doctor before use if pregnant or nursing.

Keep Oot Of Reach Of Children

Keep out of reach of children.
Do not use if tamper evident seal is broken.In case of ingestion call Poison Control Center hotline immediately at 1-800-222-1222.

Directions

Apply to the affected areas 2-3 times daily, gently massage until fully absorbed, and wait for the area to dry.

Other information

Do not use if tamper evident seal is broken.In case of ingestion call Poison Control Center hotline immediately at 1-800-222-1222.
The letters HPUS indicate that the components in this product are officially monographed in the Homeopathic Pharmacopeia of the United States.

Inactive ingredients

Alcohol, carbomer, purifed water,Arnica.sodium hydroxide,Vitamin B6, Vitamin E, Vanillyl butyl ether,MSM, Aloe vera